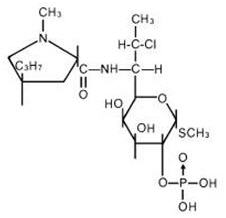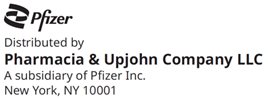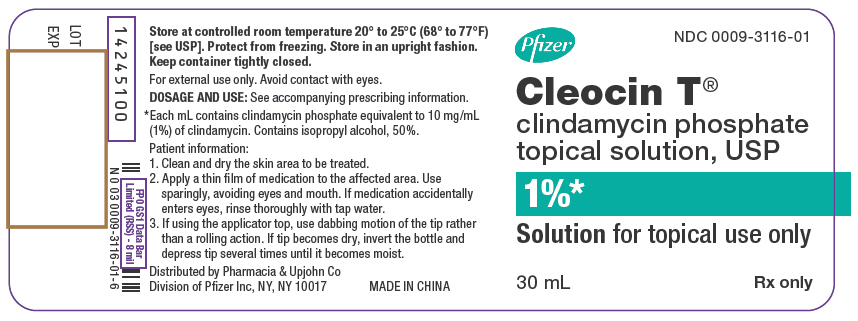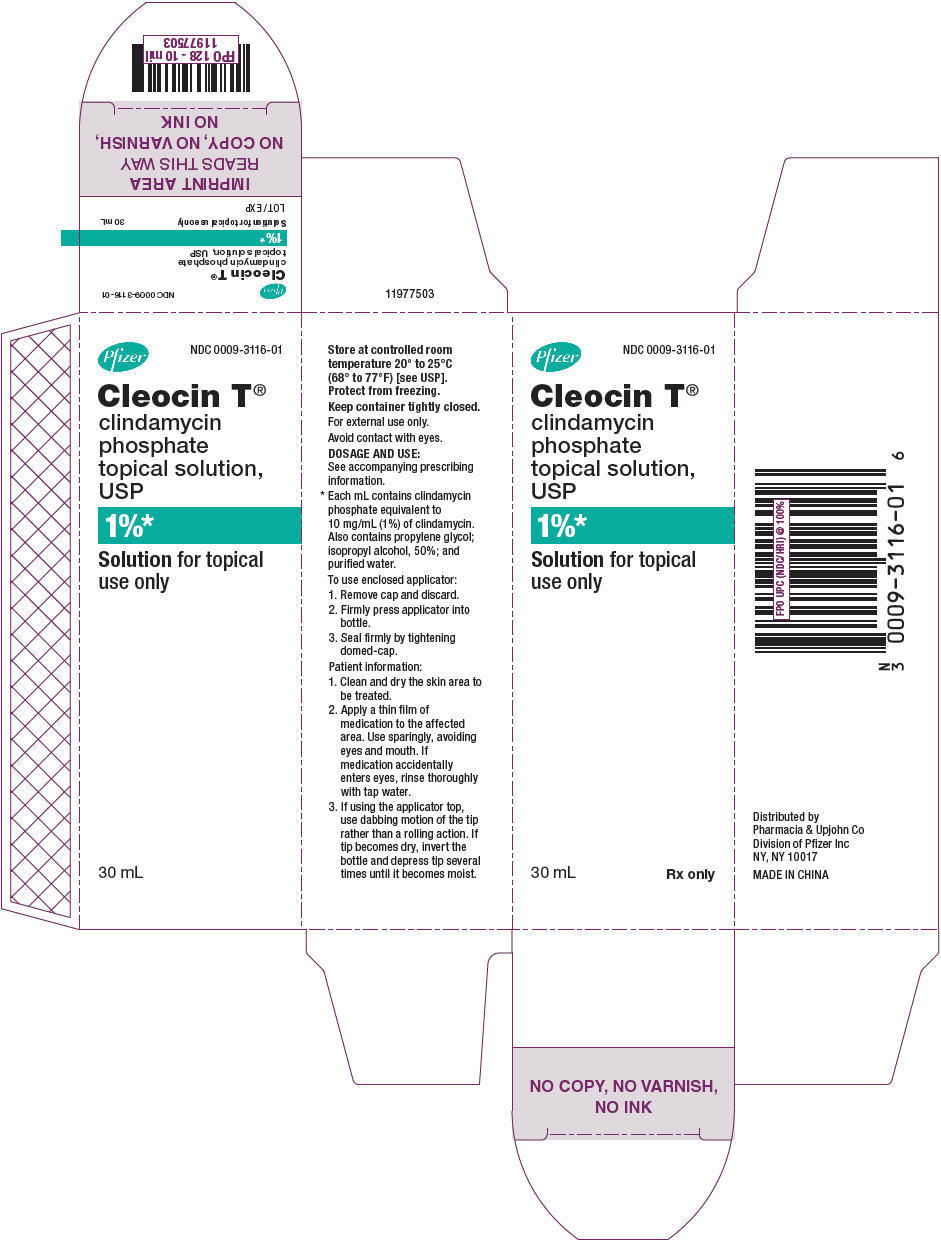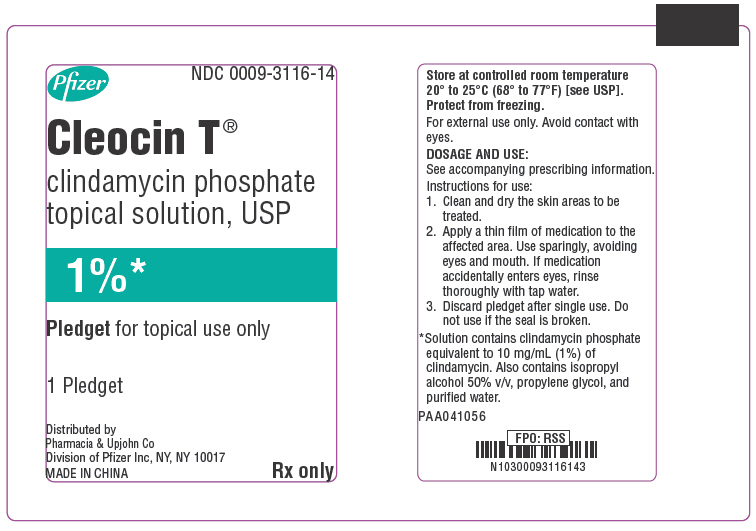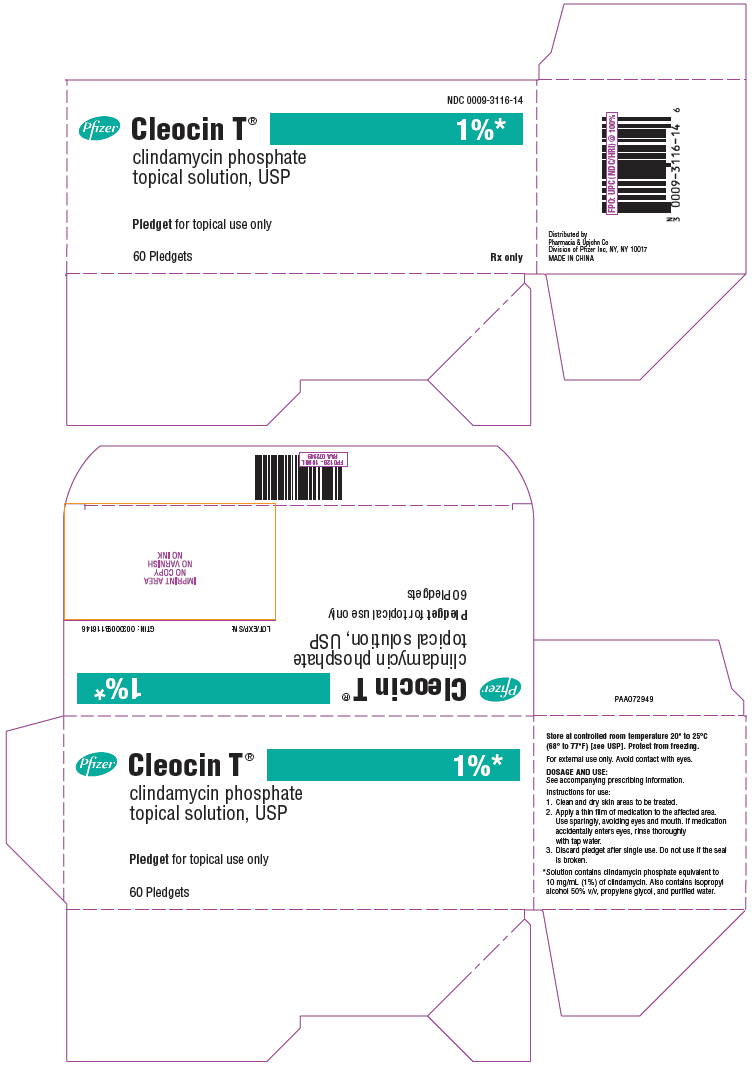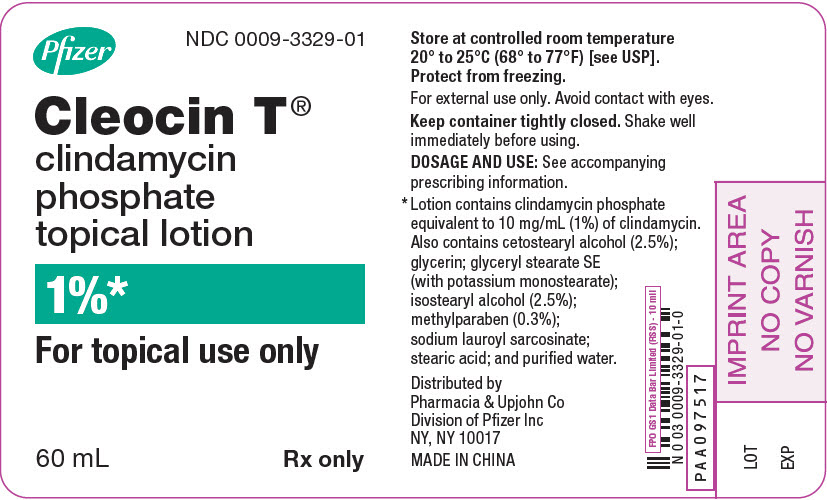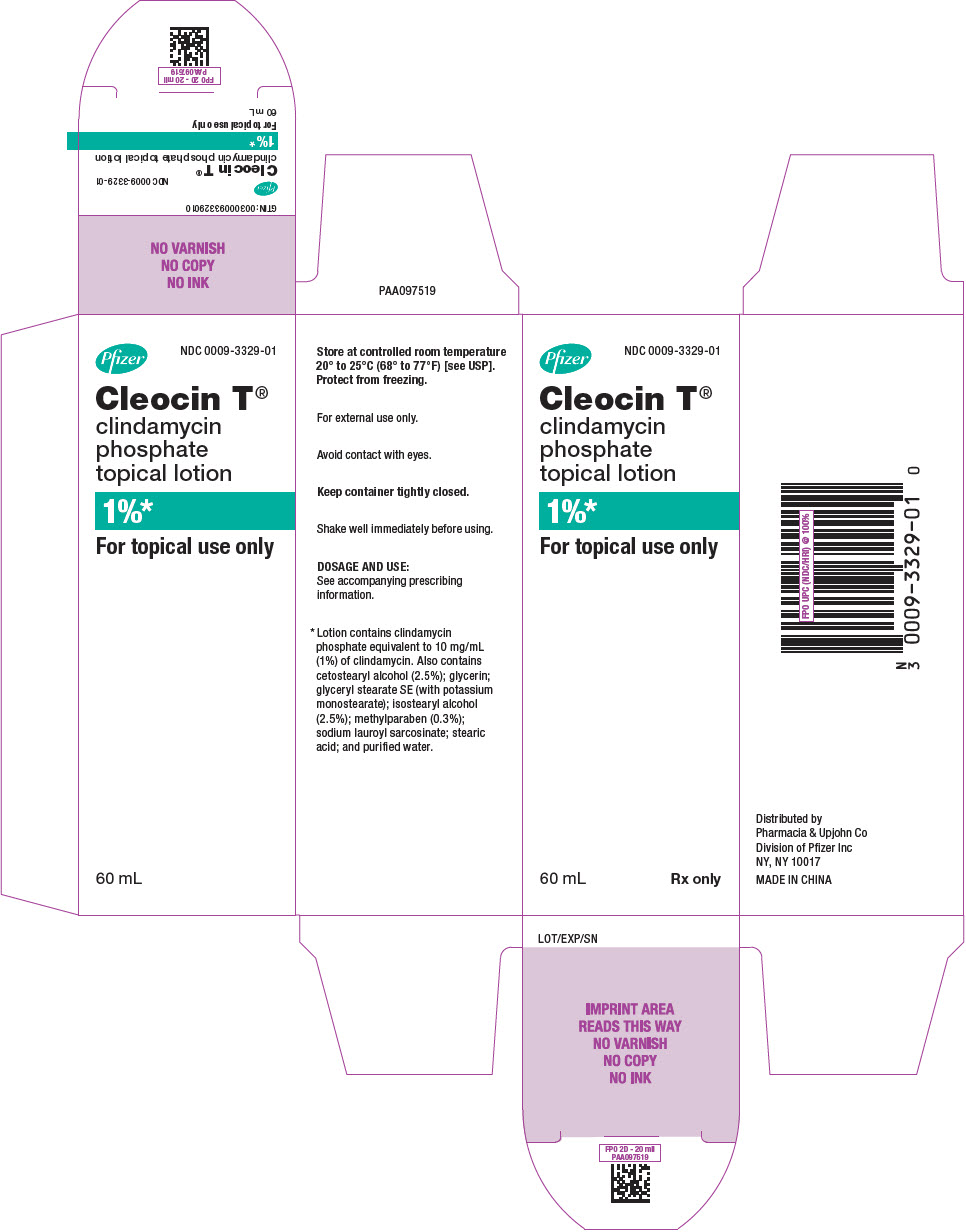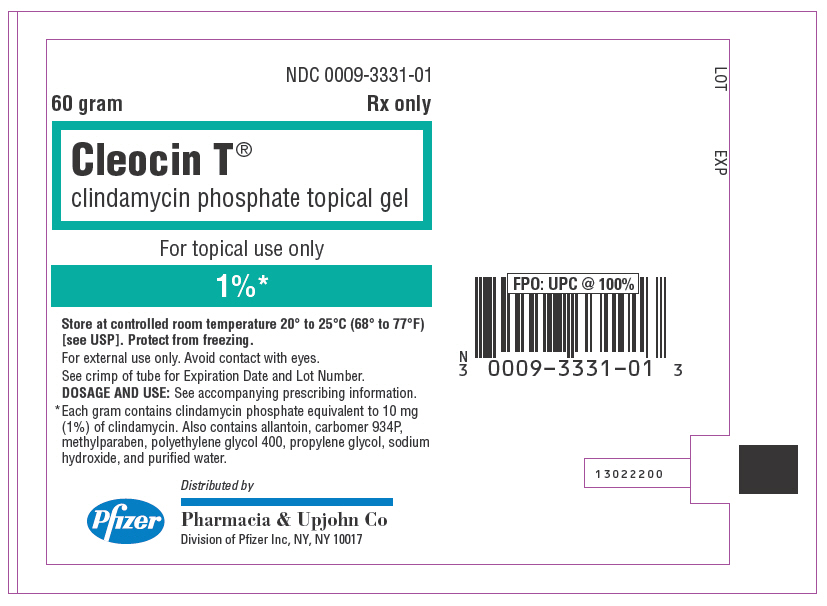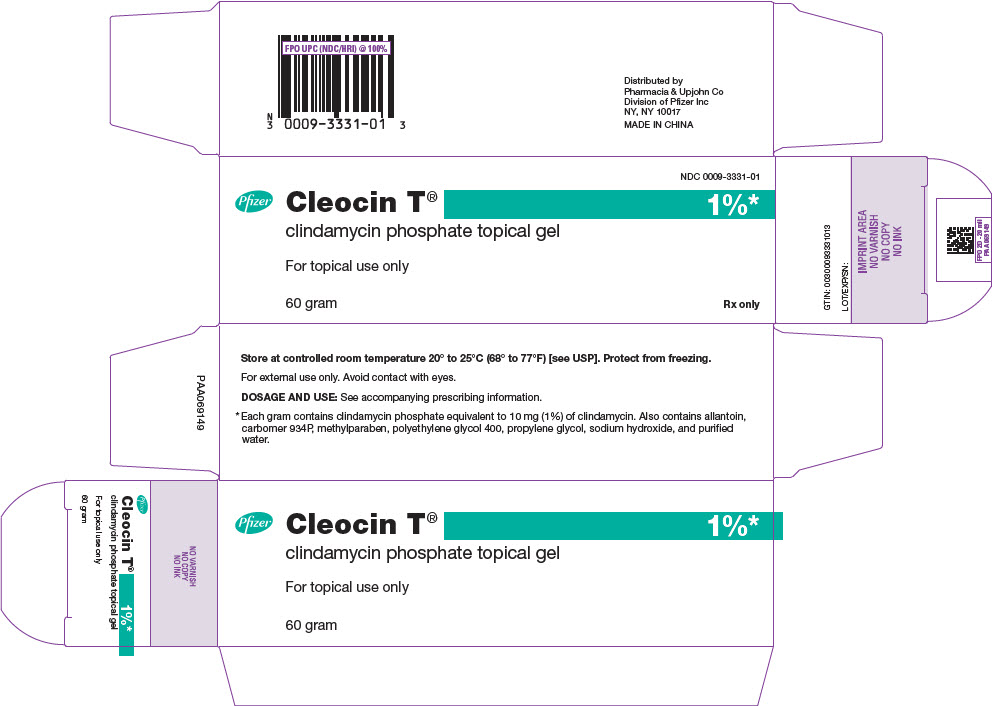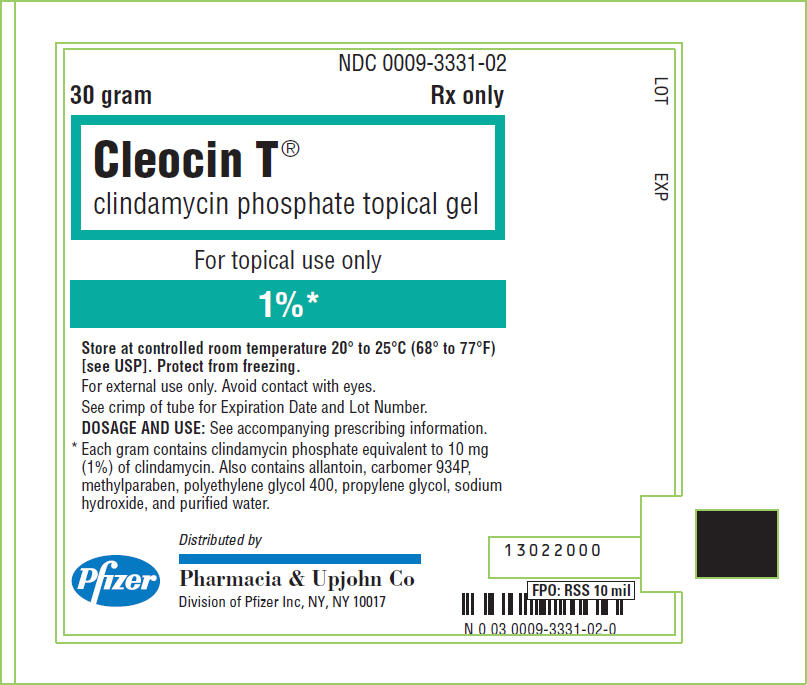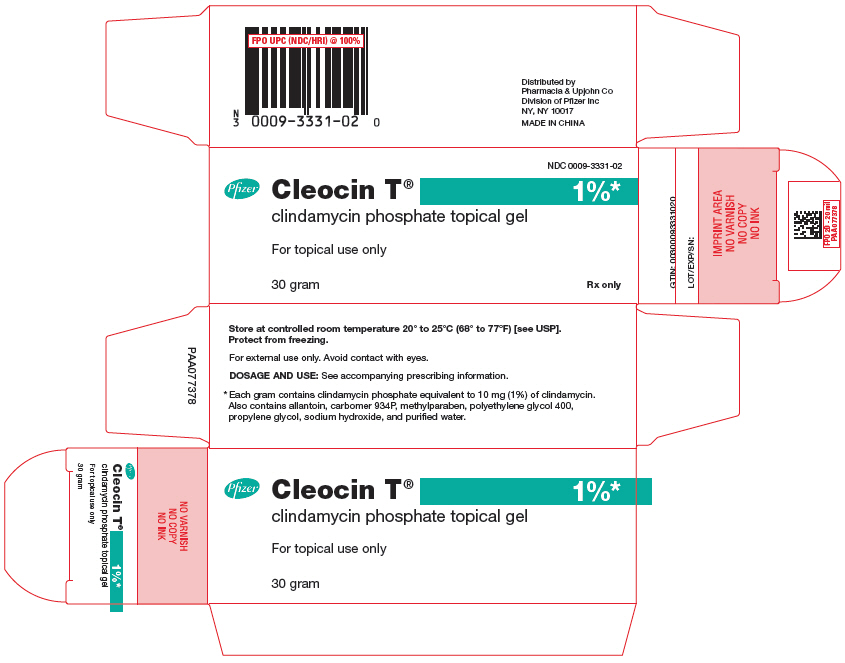 DRUG LABEL: Cleocin T
NDC: 0009-3116 | Form: SOLUTION
Manufacturer: Pharmacia & Upjohn Company LLC
Category: prescription | Type: HUMAN PRESCRIPTION DRUG LABEL
Date: 20251124

ACTIVE INGREDIENTS: CLINDAMYCIN PHOSPHATE 10 mg/1 mL
INACTIVE INGREDIENTS: ISOPROPYL ALCOHOL; PROPYLENE GLYCOL; WATER

Cleocin T®
(clindamycin phosphate topical solution, USP)
(clindamycin phosphate topical gel)
(clindamycin phosphate topical lotion)

For External Use

DESCRIPTION

CLEOCIN T Topical Solution and CLEOCIN T Topical Lotion contain clindamycin phosphate, USP, at a concentration equivalent to 10 mg clindamycin per milliliter. CLEOCIN T Topical Gel contains clindamycin phosphate, USP, at a concentration equivalent to 10 mg clindamycin per gram. Each CLEOCIN T Topical Solution pledget applicator contains approximately 1 mL of topical solution.

Clindamycin phosphate is a water soluble ester of the semi-synthetic antibacterial drug produced by a 7(S)-chloro-substitution of the 7(R)-hydroxyl group of the parent compound lincomycin.

The solution contains isopropyl alcohol 50% v/v, propylene glycol, and water.

The gel contains allantoin, carbomer 934P, methylparaben, polyethylene glycol 400, propylene glycol, sodium hydroxide, and purified water.

The lotion contains cetostearyl alcohol (2.5%); glycerin; glyceryl stearate SE (with potassium monostearate); isostearyl alcohol (2.5%); methylparaben (0.3%); sodium lauroyl sarcosinate; stearic acid; and purified water.

The structural formula is represented below:

The chemical name for clindamycin phosphate is Methyl 7-chloro-6,7,8-trideoxy-6-(1-methyl-trans-4-propyl-L-2-pyrrolidinecarboxamido)-1-thio-L-threo-α-D-galacto-octopyranoside 2-(dihydrogen phosphate).

CLINICAL PHARMACOLOGY

Mechanism of Action

The mechanism of action of clindamycin in treating acne vulgaris is unknown.

Pharmacokinetics

Following multiple topical applications of clindamycin phosphate at a concentration equivalent to 10 mg clindamycin per mL in an isopropyl alcohol and water solution, very low levels of clindamycin are present in the serum (0–3 ng/mL) and less than 0.2% of the dose is recovered in urine as clindamycin.

Although clindamycin phosphate is inactive in vitro, rapid in vivo hydrolysis converts this compound to the antibacterially active clindamycin.

Microbiology

Clindamycin inhibits bacterial protein synthesis by binding to the 23S RNA of the 50S subunit of the ribosome. Clindamycin is bacteriostatic.

Antimicrobial Activity

Clindamycin is active in vitro against most isolates of Propionibacterium acnes; however, the clinical significance is unknown.

Resistance

Resistance to clindamycin is most often caused by modification of specific bases of the 23S ribosomal RNA. Cross-resistance between clindamycin and lincomycin is complete. Because the binding sites for these antibacterial drugs overlap, cross-resistance is sometimes observed among lincosamides, macrolides and streptogramin B. Macrolide-inducible resistance to clindamycin occurs in some isolates of macrolide-resistant bacteria.

INDICATIONS AND USAGE

CLEOCIN T Topical Solution, CLEOCIN T Topical Gel and CLEOCIN T Topical Lotion are indicated in the treatment of acne vulgaris. In view of the potential for diarrhea, bloody diarrhea and pseudomembranous colitis, the physician should consider whether other agents are more appropriate (see CONTRAINDICATIONS, WARNINGS and ADVERSE REACTIONS).

CONTRAINDICATIONS

CLEOCIN T Topical Solution, CLEOCIN T Topical Gel and CLEOCIN T Topical Lotion are contraindicated in individuals with a history of hypersensitivity to preparations containing clindamycin or lincomycin, a history of regional enteritis or ulcerative colitis, or a history of antibiotic-associated colitis.

WARNINGS

Orally and parenterally administered clindamycin has been associated with severe colitis which may result in patient death. Use of the topical formulation of clindamycin results in systemic absorption from the skin surface. Diarrhea, bloody diarrhea, and colitis (including pseudomembranous colitis) have been reported with the use of topical and systemic clindamycin.

Studies indicate a toxin(s) produced by clostridia is one primary cause of antibiotic-associated colitis. The colitis is usually characterized by severe persistent diarrhea and severe abdominal cramps and may be associated with the passage of blood and mucus. Endoscopic examination may reveal pseudomembranous colitis. Stool culture for Clostridioides difficile and stool assay for C. difficile toxin may be helpful diagnostically.

When significant diarrhea occurs, the drug should be discontinued. Large bowel endoscopy should be considered to establish a definitive diagnosis in cases of severe diarrhea.

Antiperistaltic agents such as opiates and diphenoxylate with atropine may prolong and/or worsen the condition. Vancomycin has been found to be effective in the treatment of antibiotic-associated pseudomembranous colitis produced by Clostridioides difficile. The usual adult dosage is 500 milligrams to 2 grams of vancomycin orally per day in three to four divided doses administered for 7 to 10 days. Cholestyramine or colestipol resins bind vancomycin in vitro. If both a resin and vancomycin are to be administered concurrently, it may be advisable to separate the time of administration of each drug.

Diarrhea, colitis, and pseudomembranous colitis have been observed to begin up to several weeks following cessation of oral and parenteral therapy with clindamycin.

PRECAUTIONS

General

CLEOCIN T Topical Solution contains an alcohol base which will cause burning and irritation of the eye. In the event of accidental contact with sensitive surfaces (eye, abraded skin, mucous membranes), bathe with copious amounts of cool tap water. The solution has an unpleasant taste and caution should be exercised when applying medication around the mouth.

CLEOCIN T should be prescribed with caution in atopic individuals.

Drug Interactions

Clindamycin has been shown to have neuromuscular blocking properties that may enhance the action of other neuromuscular blocking agents. Therefore, it should be used with caution in patients receiving such agents.

Pregnancy:

Teratogenic Effects

In clinical trials with pregnant women, the systemic administration of clindamycin during the second and third trimesters has not been associated with an increased frequency of congenital abnormalities. There are no adequate studies in pregnant women during the first trimester of pregnancy. Clindamycin should be used during the first trimester of pregnancy only if clearly needed.

Nursing Mothers

It is not known whether clindamycin is excreted in breast milk following use of CLEOCIN T. However, orally and parenterally administered clindamycin has been reported to appear in breast milk. Clindamycin has the potential to cause adverse effects on the breast-fed infant's gastrointestinal flora. Monitor the breast-fed infant for possible adverse effects on the gastrointestinal flora, such as diarrhea, candidiasis (thrush, diaper rash) or rarely, blood in the stool indicating possible antibiotic-associated colitis.

The developmental and health benefits of breastfeeding should be considered along with the mother's clinical need for clindamycin and any potential adverse effects on the breast-fed child from clindamycin or from the underlying maternal condition.

Clinical Considerations

If used during lactation and CLEOCIN T is applied to the chest, care should be taken to avoid accidental ingestion by the infant.

Pediatric Use

Safety and effectiveness in pediatric patients under the age of 12 have not been established.

Geriatric Use

Clinical studies for CLEOCIN T did not include sufficient numbers of subjects aged 65 and over to determine whether they respond differently from younger subjects. Other reported clinical experience has not identified differences in responses between the elderly and younger patients.

ADVERSE REACTIONS

In 18 clinical studies of various formulations of CLEOCIN T using placebo vehicle and/or active comparator drugs as controls, patients experienced a number of treatment emergent adverse dermatologic events [see table below].

Number of Patients Reporting Events
Treatment Emergent Adverse Event | Solution n=553(%) | Gel n=148(%) | Lotion n=160(%)
Burning | 62 (11) | 15 (10) | 17 (11)
Itching | 36 (7) | 15 (10) | 17 (11)
Burning/Itching | 60 (11) | # (–) | # (–)
Dryness | 105 (19) | 34 (23) | 29 (18)
Erythema | 86 (16) | 10 (7) | 22 (14)
Oiliness/Oily Skin | 8 (1) | 26 (18) | 12 [of 126 subjects] (10)
Peeling | 61 (11) | # (–) | 11 (7)
# not recorded

Orally and parenterally administered clindamycin has been associated with severe colitis which may end fatally.

Cases of diarrhea, bloody diarrhea and colitis (including pseudomembranous colitis) have been reported as adverse reactions in patients treated with oral and parenteral formulations of clindamycin and rarely with topical clindamycin (see WARNINGS).

Abdominal pain, gastrointestinal disturbances, gram-negative folliculitis, eye pain and contact dermatitis have also been reported in association with the use of topical formulations of clindamycin.

OVERDOSAGE

Topically applied CLEOCIN T can be absorbed in sufficient amounts to produce systemic effects (see WARNINGS).

DOSAGE AND ADMINISTRATION

Apply a thin film of, CLEOCIN T Topical Lotion, CLEOCIN T Topical Gel, CLEOCIN T Topical Solution, or use a CLEOCIN T Topical Solution pledget for the application of CLEOCIN T twice daily to affected area. More than one pledget may be used. Each pledget should be used only once and then be discarded.

CLEOCIN T Topical Solution is flammable. Avoid fire, flame, and smoking during and immediately following application.

Lotion: Shake well immediately before using.

Pledget: Remove pledget from foil just before use. Do not use if the seal is broken. Discard after single use.

Keep all liquid dosage forms in containers tightly closed.

HOW SUPPLIED

CLEOCIN T Topical Solution containing clindamycin phosphate equivalent to 10 mg clindamycin per milliliter is available in the following sizes:

30 mL applicator bottle—NDC 0009-3116-01

60 mL applicator bottle—NDC 0009-3116-02

Carton of 60 single-use pledget applicators—NDC 0009-3116-14

CLEOCIN T Topical Gel containing clindamycin phosphate equivalent to 10 mg clindamycin per gram is available in the following sizes:

60 gram tube—NDC 0009-3331-01

30 gram tube—NDC 0009-3331-02

CLEOCIN T Topical Lotion containing clindamycin phosphate equivalent to 10 mg clindamycin per milliliter is available in the following size:

60 mL plastic squeeze bottle—NDC 0009-3329-01

STORAGE AND HANDLING

Store at controlled room temperature 20° to 25°C (68° to 77°F) [see USP].

Protect from freezing.

CLEOCIN T Topical Solution is flammable. Keep away from heat, sparks or open flames.

Rx only

This product's label may have been updated. For current full prescribing information, please visit www.pfizer.com.

LAB-0042-11.0
Revised 11/2025

PRINCIPAL DISPLAY PANEL - 30 mL Bottle Label

Pfizer

NDC 0009-3116-01

Cleocin T®
clindamycin phosphate
topical solution, USP

1%*

Solution for topical use only

30 mL

Rx only

PRINCIPAL DISPLAY PANEL - 30 mL Bottle Carton

Pfizer

NDC 0009-3116-01

Cleocin T®
clindamycin
phosphate
topical solution,
USP

1%*

Solution for topical
use only

30 mL
Rx only

PRINCIPAL DISPLAY PANEL - Pledget Packet

Pfizer

NDC 0009-3116-14

Cleocin T®
clindamycin phosphate
topical solution, USP

1%*

Pledget for topical use only

1 Pledget

Distributed by
Pharmacia & Upjohn Co
Division of Pfizer Inc, NY, NY 10017
MADE IN CHINA

Rx only

PRINCIPAL DISPLAY PANEL - 60 Pledget Packet Carton

NDC 0009-3116-14

Pfizer
Cleocin T®
1%*
clindamycin phosphate
topical solution, USP

Pledget for topical use only

60 Pledgets
Rx only

PRINCIPAL DISPLAY PANEL - 60 mL Bottle Label

Pfizer
NDC 0009-3329-01

Cleocin T®
clindamycin
phosphate
topical lotion

1%*

For topical use only

60 mL
Rx only

PRINCIPAL DISPLAY PANEL - 60 mL Bottle Carton

Pfizer
NDC 0009-3329-01

Cleocin T®
clindamycin
phosphate
topical lotion

1%*

For topical use only

60 mL
Rx only

PRINCIPAL DISPLAY PANEL - 60 gram Tube Label

NDC 0009-3331-01

60 gram

Rx only

Cleocin T®
clindamycin phosphate topical gel

For topical use only

1%*

Store at controlled room temperature 20° to 25°C (68° to 77°F)
[see USP]. Protect from freezing.
For external use only. Avoid contact with eyes.
See crimp of tube for Expiration Date and Lot Number.
DOSAGE AND USE: See accompanying prescribing information.
* Each gram contains clindamycin phosphate equivalent to 10 mg
(1%) of clindamycin. Also contains allantoin, carbomer 934P,
methylparaben, polyethylene glycol 400, propylene glycol, sodium
hydroxide, and purified water.

Pfizer
Distributed by
Pharmacia & Upjohn Co
Division of Pfizer Inc, NY, NY 10017

PRINCIPAL DISPLAY PANEL - 60 gram Tube Carton

NDC 0009-3331-01

Pfizer

Cleocin T®
1%*

clindamycin phosphate topical gel

For topical use only

60 gram
Rx only

PRINCIPAL DISPLAY PANEL - 30 gram Tube Label

NDC 0009-3331-02

30 gram

Rx only

Cleocin T®
clindamycin phosphate topical gel

For topical use only

1%*

Store at controlled room temperature 20° to 25°C (68° to 77°F)
[see USP]. Protect from freezing.
For external use only. Avoid contact with eyes.
See crimp of tube for Expiration Date and Lot Number.
DOSAGE AND USE: See accompanying prescribing information.
* Each gram contains clindamycin phosphate equivalent to 10 mg
(1%) of clindamycin. Also contains allantoin, carbomer 934P,
methylparaben, polyethylene glycol 400, propylene glycol, sodium
hydroxide, and purified water.

Pfizer
Distributed by
Pharmacia & Upjohn Co
Division of Pfizer Inc, NY, NY 10017

PRINCIPAL DISPLAY PANEL - 30 gram Tube Carton

NDC 0009-3331-02

Pfizer
Cleocin T®
1%*
clindamycin phosphate topical gel

For topical use only

30 gram
Rx only